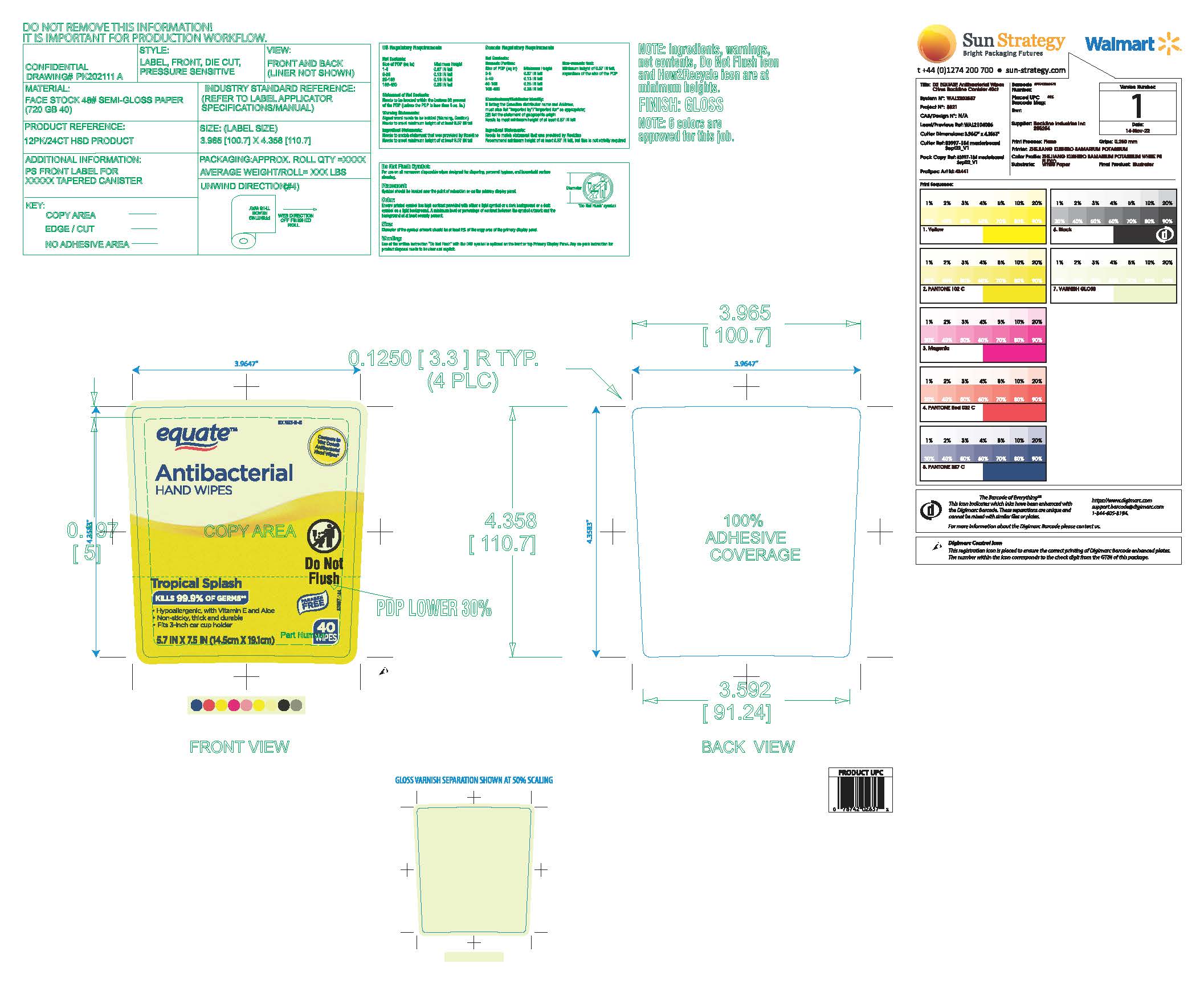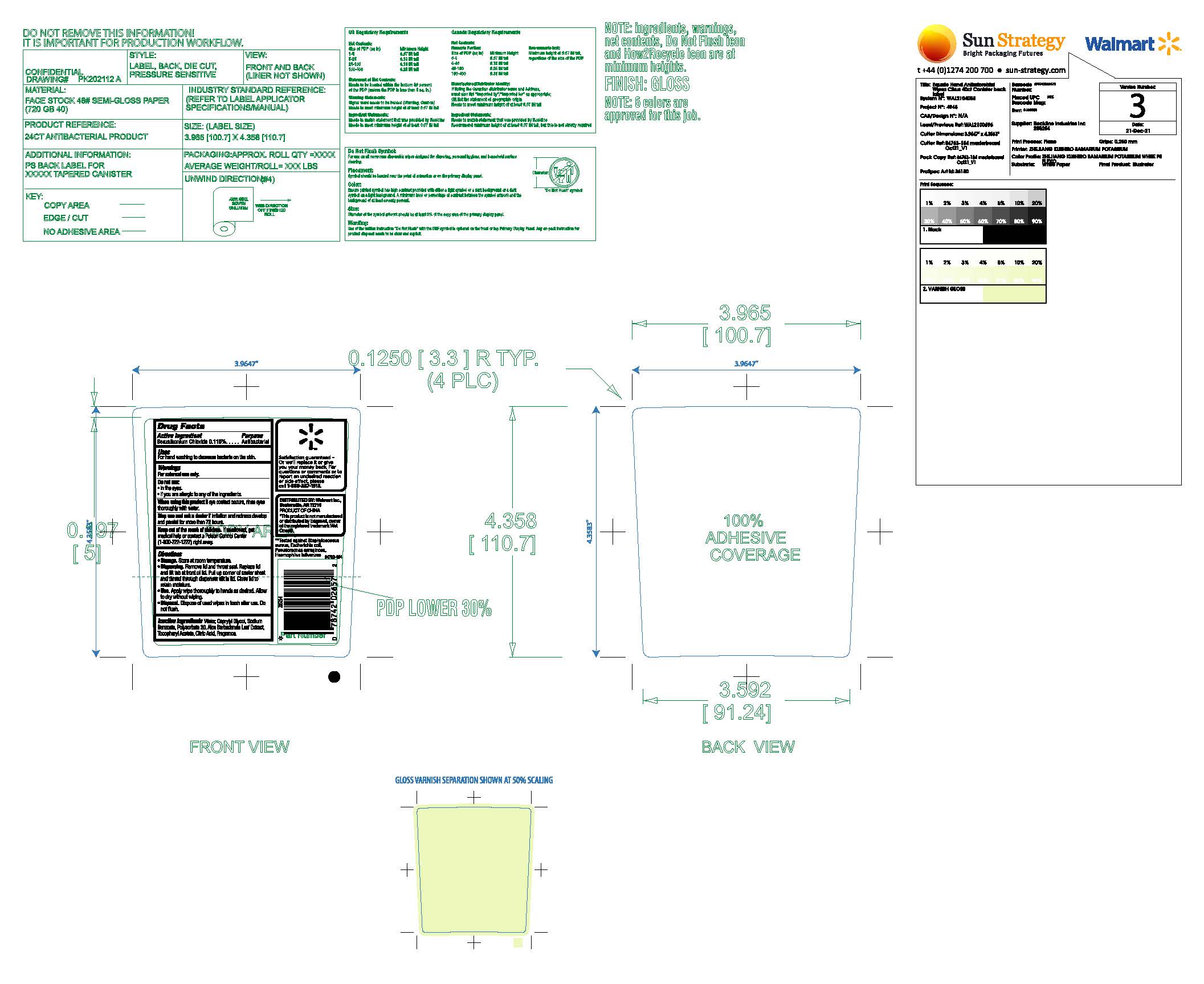 DRUG LABEL: Equate Antibacterial Citrus Hand Wipes
NDC: 79903-111 | Form: CLOTH
Manufacturer: Walmart, Inc.
Category: otc | Type: HUMAN OTC DRUG LABEL
Date: 20251001

ACTIVE INGREDIENTS: BENZALKONIUM CHLORIDE 0.115 g/1 1
INACTIVE INGREDIENTS: POLYSORBATE 20; WATER; ALOE VERA LEAF; .ALPHA.-TOCOPHEROL ACETATE; CITRIC ACID MONOHYDRATE; SODIUM BENZOATE; CAPRYLYL GLYCOL

Equate Citrus Antibac Wipes

Active Ingredient

Benzalkonium Chloride 0.115%

Purpose

Antibacterial

Uses

For handwashing to decrease bacteria on the skin

Warnings

For external use only

Do not use

- in the eyes
- if you are allergic to any of the ingredients

When using this product

if eye contact occurs, rinse eyes thoroughly with water.

Stop use and ask a doctor if

if irritation and redness develops and persist for more than 72 hours.

Keep out of reach of children

if swallowed get medical help or contact a Poison Control Center (1-800-222-1222) right away.

Directions

- Storage, Store at room temperature
- Dispensing Remove lid and throat seal. Replace lid and lift tab at front of lid. Pull up corner of center sheet and thread through dispenser slit in lid. Close lid to retain moisture.
- Use. Apply wipe thoroughly to hands as desired. Allow to dry without wiping.
- Disposal. Dispose of used wipes in a trash receptacle after use. Do not flush.

Inactive ingredients

Water, Caprylyl Glycol, Sodium Benzoate, Polysorbate 20, Aloe Barbadensis Leaf Extract, Tocopheryl Acetate, Citric Acid, Fragrance